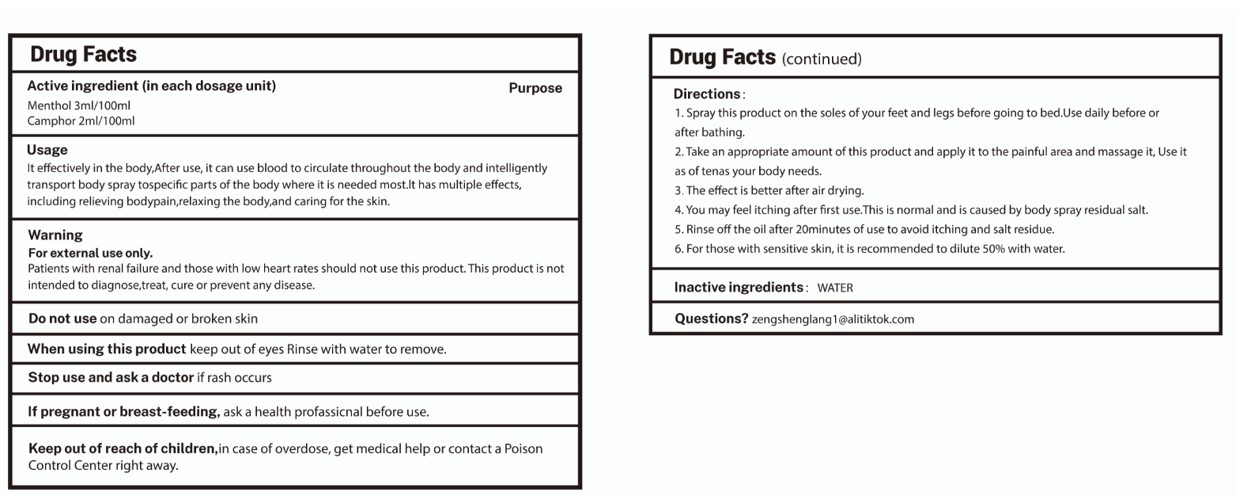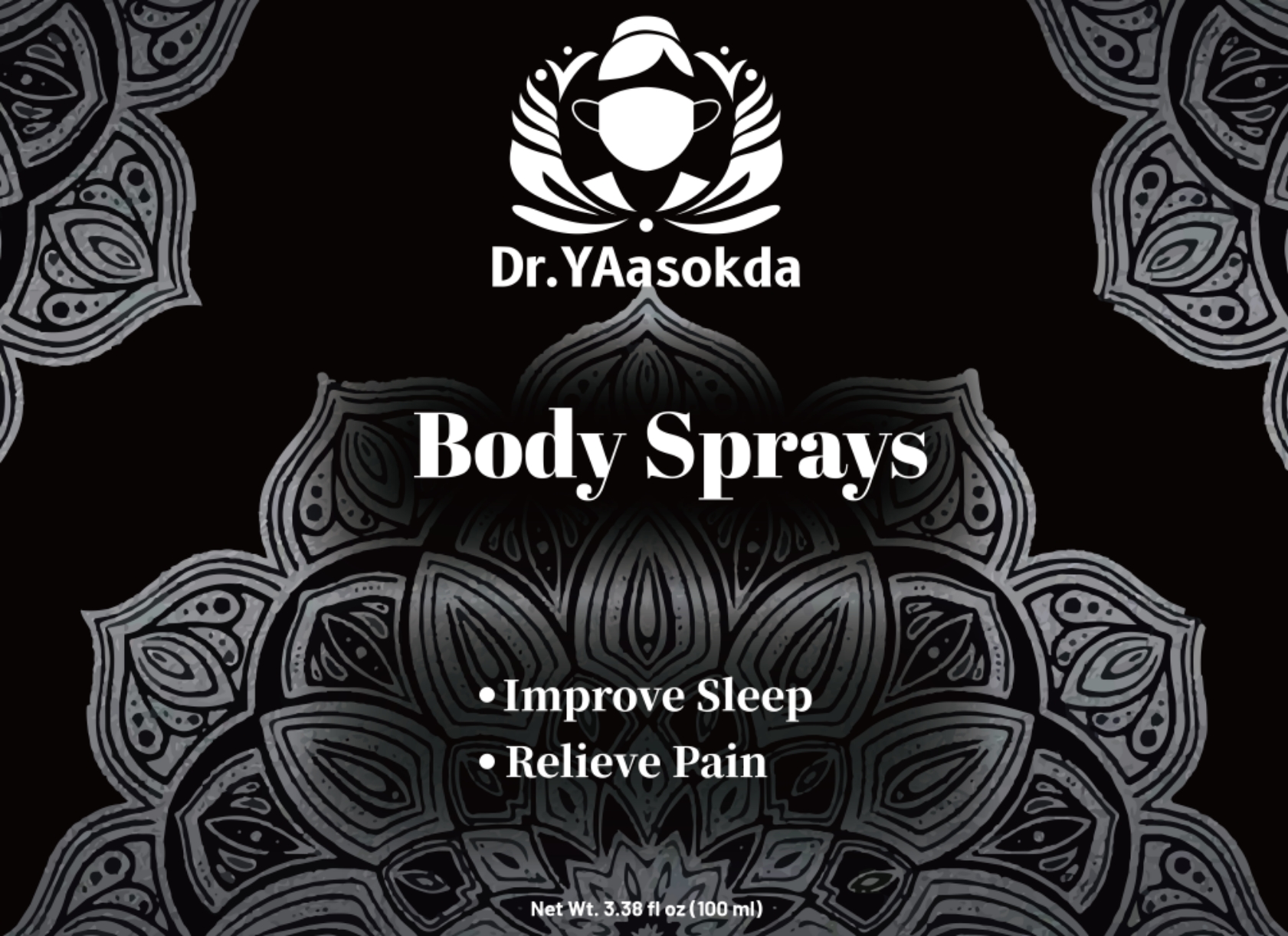 DRUG LABEL: Body Sprays
NDC: 84575-001 | Form: LIQUID
Manufacturer: Linhe Biotechnology (Shenzhen) Co., Ltd
Category: otc | Type: HUMAN OTC DRUG LABEL
Date: 20240726

ACTIVE INGREDIENTS: CAMPHOR, (-)- 2 g/100 mL; MENTHOL 3 g/100 mL
INACTIVE INGREDIENTS: WATER

Body Spray

ACTIVE INGREDIENT

Menthol 3%
Camphor 2%

PURPOSE

Improve Sleep
Relieve Pain

Keep out of reach of children,in case of overdose, get medical help or contact a PoisonControl Center right away.

INDICATIONS AND USAGE

It effectively in the body,After use, it can use blood to circulate throughout the body and intelligentlytransport body spray tospecifc parts of the body where it is needed most.t has multiple effectsincluding relieving bodypain,relaxing the body,and caring for the skin.

WARNINGS

For external use only.
Patients with renal failure and those with low heart rates should not use this product. This product is notintended to diagnose,treat, cure or prevent any disease.

DOSAGE AND ADMINISTRATION

1. Spray this product on the soles of your feet and legs before going to bed.Use daily before or
after bathing.2. Take an appropriate amount of this product and apply it to the painful area and massage it, Use itas of tenas your body needs.
3. The effect is better after air drying.
4. You may feel itching after frst use.This is normal and is caused by body spray residual salt.
5. Rinse off the oil after 20minutes of use to avoid itching and salt residue.
6. For those with sensitive skin, it is recommended to dilute 50% with water.

INACTIVE INGREDIENT

WATER

STORAGE AND HANDLING

Store in a cool and dark place away from light